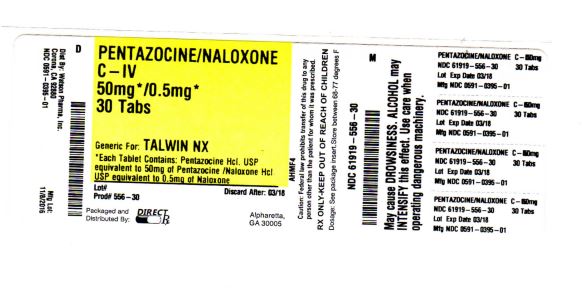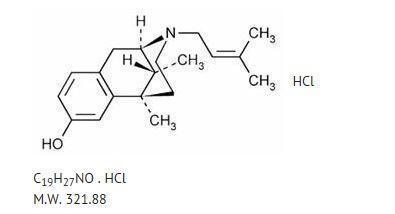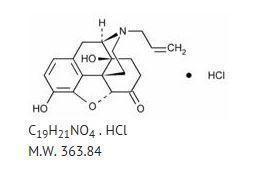 DRUG LABEL: PENTAZOCINE HYDROCHLORIDE AND NALOXONE HYDROCHLORIDE
NDC: 61919-556 | Form: TABLET
Manufacturer: DIRECT RX
Category: prescription | Type: HUMAN PRESCRIPTION DRUG LABEL
Date: 20161110
DEA Schedule: CIV

ACTIVE INGREDIENTS: PENTAZOCINE HYDROCHLORIDE 50 mg/1 1; NALOXONE HYDROCHLORIDE 0.5 mg/1 1
INACTIVE INGREDIENTS: SILICON DIOXIDE; D&C YELLOW NO. 10; DIBASIC CALCIUM PHOSPHATE DIHYDRATE; SODIUM LAURYL SULFATE; MAGNESIUM STEARATE; CELLULOSE, MICROCRYSTALLINE; STARCH, CORN

PENTAZOCINE HYDROCHLORIDE AND NALOXONE HYDROCHLORIDE

BOXED WARNING SECTION

WARNING: Pentazocine Hydrochloride and Naloxone Hydrochloride Tablets, USP is intended for oral use only. Severe, potentially lethal, reactions may result from misuse of Pentazocine Hydrochloride and Naloxone Hydrochloride Tablets, USP by injection either alone or in combination with other substances. (See DRUG ABUSE AND DEPENDENCE section.)

DESCRIPTION SECTION

Pentazocine Hydrochloride and Naloxone Hydrochloride Tablets contains pentazocine hydrochloride, USP, equivalent to 50 mg base and is a member of the benzazocine series (also known as the benzomorphan series), and naloxone hydrochloride, USP, equivalent to 0.5 mg base.

Pentazocine Hydrochloride and Naloxone Hydrochloride Tablets, USP is an analgesic for oral administration.

Chemically, pentazocine hydrochloride is (2R*,6R*,11R*)-1,2,3,4,5,6-Hexahydro-6,11dimethyl-3-(3-methyl-2-butenyl)-2,6-methano-3-benzazocin-8-ol hydrochloride, a white, crystalline substance soluble in acidic aqueous solutions, and has the following structural formula:

Chemically, naloxone hydrochloride is Morphinan-6-one,4,5-epoxy-3,14-dihydroxy-17-(2propenyl)-, hydrochloride, (5α)-. It is a slightly off-white powder, and is soluble in water and dilute acids, and has the following structural formula:

CLINICAL PHARMACOLOGY SECTION

Pentazocine is a Schedule IV opioid analgesic which when administered orally in a 50 mg dose appears equivalent in analgesic effect to 60 mg of codeine.

Pentazocine weakly antagonizes the analgesic effects of morphine and meperidine; in addition, it produces incomplete reversal of cardiovascular, respiratory, and behavioral depression induced by morphine and meperidine. Pentazocine has about 1/50 the antagonistic activity of nalorphine. It also has sedative activity.

Onset of significant analgesia usually occurs between 15 and 30 minutes after oral administration, and duration of action is usually three hours or longer.

Pentazocine is well absorbed from the gastrointestinal tract. Concentrations in plasma coincide closely with the onset, duration, and intensity of analgesia. The time to mean peak concentration in 24 normal volunteers was 1.7 hours (range 0.5 to 4 hours) after oral administration and the mean plasma elimination half-life was 3.6 hours (range 1.5 to 10 hours).

Pentazocine is metabolized in the liver and excreted primarily in the urine. The products of the oxidation of the terminal methyl groups and glucuronide conjugates are excreted by the kidney. Elimination of approximately 60% of the total dose occurs within 24 hours. Pentazocine passes into the fetal circulation.

Naloxone when administered orally at 0.5 mg has no pharmacologic activity. Naloxone hydrochloride administered parenterally at the same dose is an antagonist to pentazocine and a pure antagonist to narcotic analgesics.

Pentazocine hydrochloride and naloxone hydrochloride is a potent analgesic when administered orally. However, the presence of naloxone in Pentazocine hydrochloride and naloxone hydrochloride is intended to prevent the effect of pentazocine if the product is misused by injection.

Studies in animals indicate that the presence of naloxone does not affect pentazocine analgesia when the combination is given orally. If the combination is given by injection the action of pentazocine is neutralized.

INDICATIONS & USAGE SECTION

Pentazocine Hydrochloride and Naloxone Hydrochloride Tablets, USP is indicated for the relief of moderate to severe pain.

Pentazocine Hydrochloride and Naloxone Hydrochloride Tablets, USP is indicated for oral use only.

CONTRAINDICATIONS SECTION

Pentazocine hydrochloride and naloxone hydrochloride tablets is contraindicated in patients who are hypersensitive to either pentazocine or naloxone.

DRUG ABUSE AND DEPENDENCE SECTION

Pentazocine can cause a physical and psychological dependence. (See DRUG ABUSE AND DEPENDENCE.)

Use In Head Injury and Increased Intracranial Pressure

In the presence of head injury, intracranial lesions or a preexisting increase in intracranial pressure, the possible respiratory depressant effects of pentazocine and its potential to elevate cerebrospinal fluid pressure (resulting from vasodilation following CO2 retention) may be markedly increased. Furthermore, pentazocine can produce effects on pupillary response and consciousness, which may obscure neurologic signs of further increases in intracranial pressure in patients with head injuries. In such patients, pentazocine must be used with extreme caution and only if its use is deemed essential.

Interactions with Alcohol and Drugs of Abuse

Pentazocine may be expected to have additive effects when used in conjunction with alcohol, other opioids, or illicit drugs that cause central nervous system depression because respiratory depression, hypotension, profound sedation, coma or death may result.

Patients Receiving Narcotics

Pentazocine is a mild narcotic antagonist. Some patients previously given narcotics, including methadone for the daily treatment of narcotic dependence, have experienced withdrawal symptoms after receiving pentazocine.

Respiratory Depression

Respiratory depression occurs more frequently in elderly or debilitated patients and in those suffering from conditions accompanied by hypoxia, hypercapnia, or upper airway obstruction, in whom even moderate therapeutic doses may significantly decrease pulmonary ventilation. Use pentazocine hydrochloride and naloxone hydrochloride with extreme caution in patients with chronic obstructive pulmonary disease or cor pulmonale and in patients having a substantially decreased respiratory reserve (e.g., severe kyphoscoliosis), hypoxia, hypercapnia, or pre-existing respiratory depression. Alternative non-opioid analgesics should be considered, and pentazocine hydrochloride and naloxone hydrochloride should be employed only under careful medical supervision at the lowest effective dose in such patients.

Acute CNS Manifestations

Patients receiving therapeutic doses of pentazocine hydrochloride and naloxone hydrochloride have experienced hallucinations (usually visual), disorientation, and confusion which have cleared spontaneously within a period of hours. The mechanism of this reaction is not known. Such patients should be very closely observed and vital signs checked. If the drug is reinstituted, it

PRECAUTIONS SECTION

- Drug Abuse and Dependence
  Pentazocine hydrochloride and naloxone hydrochloride tablets are Schedule IV controlled substance.
  Abuse and addiction are separate and distinct from physical dependence and tolerance. Abuse is characterized by misuse of a drug for non-medical purposes, often in combination with other psychoactive substances. Addiction is a disease of repeated drug abuse. Addiction is a primary, chronic, neurobiologic disease, with genetic, psychosocial, and environmental factors influencing its development and manifestations. Addiction is characterized by behaviors that include one or more of the following: impaired control over drug use, compulsive use, continued use despite harm, and craving. Drug addiction is a treatable disease, utilizing a multidisciplinary approach, but relapse is common. Physical dependence is a state of adaptation that is manifested by a specific withdrawal syndrome that can be produced by abrupt cessation, rapid dose reduction, decreasing blood level of the drug, and/or administration of an antagonist. Tolerance is a state of adaptation in which exposure to a drug induces changes that result in a diminution of one or more of the drug’s effects over time. Tolerance may occur to both the desired and undesired effects of drugs, and may develop at different rates for different effects.
  Physicians should be aware that addiction may not be accompanied by concurrent tolerance and symptoms of physical dependence in all addicts. In addition, abuse of opioids can occur in the absence of addiction and is characterized by misuse of the drug for non-medical purposes, and often in combination with other psychoactive substances.
  There have been some reports of dependence and of withdrawal symptoms with pentazocine hydrochloride and naloxone hydrochloride. Patients with a history of drug dependence should be under close supervision while receiving Pentazocine hydrochloride and naloxone hydrochloride. There have been rare reports of possible abstinence syndromes in newborns after prolonged use of pentazocine hydrochloride and naloxone hydrochloride during pregnancy.
  There have been reports of development of addiction and physical dependence in patients receiving parenteral pentazocine. People with a history of drug abuse or alcohol abuse may have a higher chance of becoming addicted to opioid medicines.
  Abrupt dose cessation or rapid dose reduction following the extended use of parenteral pentazocine has resulted in withdrawal symptoms such as abdominal cramps, nausea, vomiting, elevated temperature, chills, rhinorrhea, restlessness, anxiety, or lacrimation. In general opioid therapy should not be abruptly discontinued. When the patient no longer requires treatment with pentazocine hydrochloride and naloxone hydrochloride, the drug should be tapered gradually to prevent signs and symptoms of withdrawal in patients who have been receiving opioids for an extended period of time and might have become physically dependent.
  In prescribing pentazocine hydrochloride and naloxone hydrochloride for chronic use, the physician should take under consideration that proper assessment of the patient, proper prescribing practices, periodic re-evaluation of therapy, and proper dispensing and storage are appropriate measures that help to identify and decrease misuse and abuse of opioid drugs.
  The amount of naloxone present in pentazocine hydrochloride and naloxone hydrochloride (0.5 mg per tablet) has no action when taken orally and will not interfere with the pharmacologic action of pentazocine. However, this amount of naloxone given by injection has profound antagonistic action to narcotic analgesics.
  Severe, even lethal, consequences may result from misuse of tablets by injection either alone or in combination with other substances, such as pulmonary emboli, vascular occlusion, ulceration and abscesses, and withdrawal symptoms in narcotic dependent individuals.
  CNS Effect
  Caution should be used when pentazocine hydrochloride and naloxone hydrochloride is administered to patients prone to seizures; seizures have occurred in a few such patients in association with the use of pentazocine though no cause and effect relationship has been established.
  Porphyria
  Particular caution should be exercised in administering pentazocine to patients with porphyria since it may provoke an acute attack in susceptible individuals.
  Cardiovascular Disease
  Pentazocine can elevate blood pressure, possibly through the release of endogenous catecholamines. Particular caution should be exercised in conditions where alterations in vascular resistance and blood pressure might be particularly undesirable, such as in the acute phase of myocardial infarction.
  Pentazocine hydrochloride and naloxone hydrochloride should be used with caution in patients with myocardial infarction who have nausea or vomiting.
  Impaired Renal or Hepatic Function
  Decreased metabolism of pentazocine by the liver in extensive liver disease may predispose to accentuation of side effects. Although laboratory tests have not indicated that pentazocine causes or increases renal or hepatic impairment, the drug should be administered with caution to patients with such impairment.
  Other
  Caution should also be observed when administering pentazocine hydrochloride and naloxone hydrochloride in patients with hypothyroidism, adrenocortical insufficiency, prostate hypertrophy, inflammatory or obstructive bowel disease, acute abdominal syndromes of unknown etiology, cholecystitis, pancreatitis, or acute alcohol intoxication and delirium tremens.
  Biliary Surgery
  Narcotic drug products are generally considered to elevate biliary tract pressure for varying periods following their administration. Some evidence suggests that pentazocine may differ from other marketed narcotics in this respect (i.e., it causes little or no elevation in biliary tract pressures). The clinical significance of these findings, however, is not yet known.
  Information for Patients
  - Patients receiving pentazocine hydrochloride and naloxone hydrochloride should be given the following instructions by the physician:
  - Patients should be advised that pentazocine hydrochloride and naloxone hydrochloride is a narcotic pain reliever, and should be taken only as directed.
  - The dose of pentazocine hydrochloride and naloxone hydrochloride should not be adjusted without consulting with a physician or other healthcare professional.
  - Patients should be advised that pentazocine hydrochloride and naloxone hydrochloride may cause drowsiness, dizziness, or lightheadedness and may impair mental and/or physical ability required for the performance of potentially hazardous tasks (e.g., driving, operating machinery). Patients started on pentazocine hydrochloride and naloxone hydrochloride or patients whose dose has been adjusted should refrain from any potentially dangerous activity until it is established that they are not adversely affected.
  - Pentazocine hydrochloride and naloxone hydrochloride will add to the effect of alcohol and other CNS depressants (such as antihistamines, sedatives, hypnotics, tranquilizers, general anesthetics, phenothiazines, other opioids, and monoamine oxidase [MAO]inhibitors).
  - Patients should not combine pentazocine hydrochloride and naloxone hydrochloride with alcohol or other central nervous system depressants (sleep aids, tranquilizers) except by the orders of the prescribing physician, because dangerous additive effects may occur, resulting in serious injury or death.
  - Women of childbearing potential who become or are planning to become pregnant should consult a physician prior to initiating or continuing therapy with pentazocine hydrochloride and naloxone hydrochloride.
  - Safe use in pregnancy has not been established. Prolonged use of opioid analgesics during pregnancy may cause neonatal physical dependence, and neonatal withdrawal may occur.
  - If patients have been receiving treatment with pentazocine hydrochloride and naloxone hydrochloride for more than a few weeks and cessation of therapy is indicated, they should be counseled on the importance of safely tapering the dose and that abruptly discontinuing the medication could precipitate withdrawal symptoms. The physician should provide a dose schedule to accomplish a gradual discontinuation of the medication.
  - Patients should be advised that pentazocine hydrochloride and naloxone hydrochloride is a potential drug of abuse. They should protect it from theft. It should never be given to anyone other than the individual for whom it was prescribed.
  - Patients should be instructed to keep pentazocine hydrochloride and naloxone hydrochloride in a secure place out of the reach of children. When Pentazocine hydrochloride and naloxone hydrochloride is no longer needed, please consult your pharmacist for proper disposal instructions.
  - As with other opioids, patients taking pentazocine hydrochloride and naloxone hydrochloride should be advised of the potential for severe constipation; appropriate laxatives and/or stool softeners as well as other appropriate treatments should be initiated from the onset of opioid therapy.
  - Patients should be advised of the most common adverse events that may occur while taking pentazocine hydrochloride and naloxone hydrochloride: constipation, nausea, somnolence, lightheadedness, dizziness, sedation, vomiting, and sweating.
  Drug Interactions
  CNS Depressants
  Other central nervous system (CNS) depressants including sedatives, hypnotics, general anesthetics, antiemetics, phenothiazines, or other tranquilizers or alcohol increases the risk of respiratory depression, hypotension, profound sedation, or coma. Use morphine sulfate with caution and in reduced dosages in patients taking these agents.
  Opioid Agonist Analgesics
  Pentazocine hydrochloride and naloxone hydrochloride can antagonize the effects of a pure opioid agonist analgesic and/or may precipitate withdrawal symptoms.
  Monoamine Oxidase Inhibitors (MAOIs)
  Concomitant use of monoamine oxidase inhibitors (MAOIs) with pentazocine hydrochloride and naloxone hydrochloride may cause CNS excitation and hypertension through their respective effects on catecholamines. Caution should therefore be observed in administering pentazocine hydrochloride and naloxone hydrochloride to patients who are currently receiving MAOIs or who have received them within the preceding 14 days.
  Anticholinergics
  Anticholinergics or other medications with anticholinergic activity when used concurrently with opioid analgesics may result in increased risk of urinary retention and/or severe constipation, which may lead to paralytic ileus.
  Tobacco
  Smoking tobacco could enhance the metabolic clearance rate of pentazocine reducing the clinical effectiveness of a standard dose of pentazocine.
  Carcinogenesis, Mutagenesis, Impairment of Fertility
  No long-term studies in animals to test for carcinogenesis have been performed with the components of pentazocine hydrochloride and naloxone hydrochloride.
  Studies to evaluate the mutagenic potential of the components of pentazocine hydrochloride and naloxone hydrochloride have not been conducted.
  Pentazocine, when administered orally or parenterally, had no adverse effect on either the reproductive capabilities or the course of pregnancy in rabbits and rats. Embryotoxic effects on the fetuses were not shown.
  The daily administration of 4 mg/kg to 20 mg/kg pentazocine subcutaneously to female rats during a 14 day pre-mating period and until the 13th day of pregnancy did not have any adverse effects on the fertility rate.
  Pregnancy
  Teratogenic Effects
  Pregnancy Category C
  There are no adequate and well-controlled studies in pregnant women. Pentazocine hydrochloride and naloxone hydrochloride should be used during pregnancy only if the potential benefit justifies the potential risk to the fetus.
  In a published report, a single dose of pentazocine administered to pregnant hamsters on gestation day 8 increased the incidence of exencephaly and cranioschisis at a dose of 196 mg/kg, SC (0.4-times the maximum daily human dose of pentazocine via 12 tablets on a mg/m2 basis).
  Animal reproduction studies testing the combination of pentazocine and naloxone during organogenesis have been completed in rats and rabbits. In rats, a pentazocine:naloxone dose of 64 mg/kg:0.64 mg/kg via oral gavage increased the incidences of resorptions and extra ribs (0.2-times the maximum daily human dose of pentazocine via 12 tablets on a mg/m2 basis). There were no clear treatment related effects in rabbits treated with a pentazocine:naloxone dose of up to 64 mg/kg:0.64 mg/kg via oral gavage (0.3-times the maximum daily human dose of pentazocine via 12 tablets on a mg/m2 basis).
  Nonteratogenic Effects
  There has been no experience in this regard with pentazocine hydrochloride and naloxone hydrochloride. However, there have been rare reports of possible abstinence syndromes in newborns after prolonged use of pentazocine during pregnancy.
  Labor and Delivery
  Patients receiving pentazocine during labor have experienced no adverse effects other than those that occur with commonly used analgesics. However, pentazocine can cross the placental barrier and cause central nervous system depression in the newborn and, if used regularly throughout pregnancy, may lead to symptoms of withdrawal in the newborn. pentazocine hydrochloride and naloxone hydrochloride should be used with caution in women delivering premature infants. The effect of pentazocine hydrochloride and naloxone hydrochloride on the mother and fetus, the duration of labor or delivery, the possibility that forceps delivery or other intervention or resuscitation of the newborn may be necessary, or the effect of pentazocine hydrochloride and naloxone hydrochloride on the later growth, development, and functional maturation of the child are unknown at the present time.
  Nursing Mothers
  Pentazocine is excreted in human milk. Caution should be exercised when pentazocine hydrochloride and naloxone hydrochloride is administered to a nursing woman.
  Pediatric Use
  Safety and effectiveness in pediatric patients below the age of 12 years have not been established.
  Geriatric Use
  Controlled clinical studies of pentazocine hydrochloride and naloxone hydrochloride did not include sufficient numbers of subjects aged 65 and over to determine whether they respond differently from younger subjects. Other reported clinical experience has not identified differences in responses or effectiveness in analgesic activity between the elderly and younger patients. In general, dose selection for an elderly patient should be cautious, usually starting at the low end of the dosing range, reflecting the greater frequency of decreased hepatic, renal, or cardiac function, and of concomitant disease or other drug therapy.

ADVERSE REACTIONS SECTION

Cardiovascular. Hypertension, hypotension, circulatory depression, tachycardia, syncope.

Respiratory. Rarely, respiratory depression.

Acute CNS Manifestations. Hallucinations (usually visual), disorientation, and confusion .

Other CNS Effects. Grand mal convulsions, increase in intracranial pressure, dizziness, lightheadedness, hallucinations, sedation, euphoria, headache, confusion, disorientation; infrequently weakness, disturbed dreams, insomnia, syncope, and depression; and rarely tremor, irritability, excitement, tinnitus.

Autonomic. Sweating; infrequently flushing; and rarely chills.

Gastrointestinal. Nausea, vomiting, constipation, diarrhea, anorexia, dry mouth, biliary tract spasm, and rarely abdominal distress.

Allergic. Edema of the face; anaphylactic shock; dermatitis, including pruritus; flushed skin, including plethora; infrequently rash, and rarely urticaria.

Ophthalmic. Visual blurring and focusing difficulty, miosis.

Hematologic. Depression of white blood cells (especially granulocytes), with rare cases of agranulocytosis, which is usually reversible, moderate transient eosinophilia.

Dependence and Withdrawal Symptoms. (See WARNINGS, PRECAUTIONS, and DRUG ABUSE AND DEPENDENCE Sections).

Other. Urinary retention, paresthesia, serious skin reactions, including erythema multiforme, Stevens-Johnson syndrome toxic epidermal necrolysis, and alterations in rate or strength of uterine contractions during labor.

OVERDOSAGE SECTION

Manifestations

For pentazocine alone in single doses above 60 mg there have been reports of the occurrence of nalorphine-like psychotomimetic effects such as anxiety, nightmares, strange thoughts, and hallucinations. Somnolence, marked respiratory depression associated with hypertension and tachycardia have also resulted as have seizures, hypotension, dizziness, nausea, vomiting, lethargy, and paresthesias. The respiratory depression is antagonized by naloxone (see Treatment). Circulatory failure and deepening coma may occur in more severe cases, particularly in patients who have also ingested other CNS depressants such as alcohol, sedative/hypnotics, or antihistamines.

Treatment

Adequate measures to maintain ventilation and general circulatory support should be employed. Assisted or controlled ventilation, intravenous fluids, vasopressors, and other supportive measures should be employed as indicated. Consideration should be given to gastric lavage and gastric aspiration. For respiratory depression due to overdosage or unusual sensitivity to pentazocine, parenteral naloxone is a specific and effective antagonist. Initial doses of 0.4 to 2.0 mg of naloxone are recommended, repeated at 2-3 minute intervals, if needed, up to a total of 10 mg. Anti-convulsant therapy may be necessary.

DOSAGE & ADMINISTRATION SECTION

DOSAGE AND ADMINISTRATION

Adults

The usual initial adult dose is 1 tablet every three or four hours. This may be increased to 2 tablets when needed. Total daily dosage should not exceed 12 tablets.

Discontinuation

Due to the potential for withdrawal symptoms associated with abrupt discontinuation, consideration should be given to tapering patients off pentazocine hydrochloride and naloxone hydrochloride after prolonged periods of treatment with pentazocine hydrochloride and naloxone hydrochloride (See PRECAUTIONS, Drug Abuse and Dependence).

HOW SUPPLIED SECTION

Pentazocine Hydrochloride and Naloxone Hydrochloride Tablets, USP is available as light yellow, capsule shaped tablet debossed “NL” on left side and “680” on the right side of the bisect and plain on the other side. Each tablet contains pentazocine hydrochloride equivalent to 50 mg base and naloxone hydrochloride equivalent to 0.5 mg base.

Bottles of 100 (NDC 43386-680-01).

Store at 20° C -25° C (68° - 77° F); See USP Controlled Room Temperature.

Manufactured by:

Novel Laboratories, Inc.

Somerset, NJ 08873

Distributed by:

GAVIS Pharmaceuticals, LLC

Somerset, NJ 08873

GIN-680-01

Rev: 04/2011